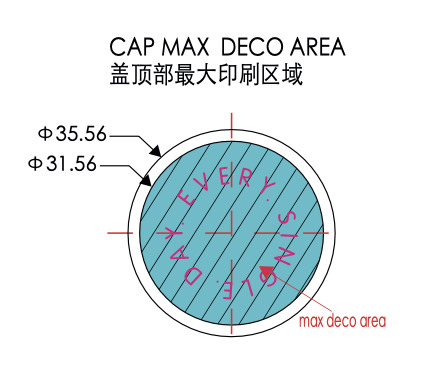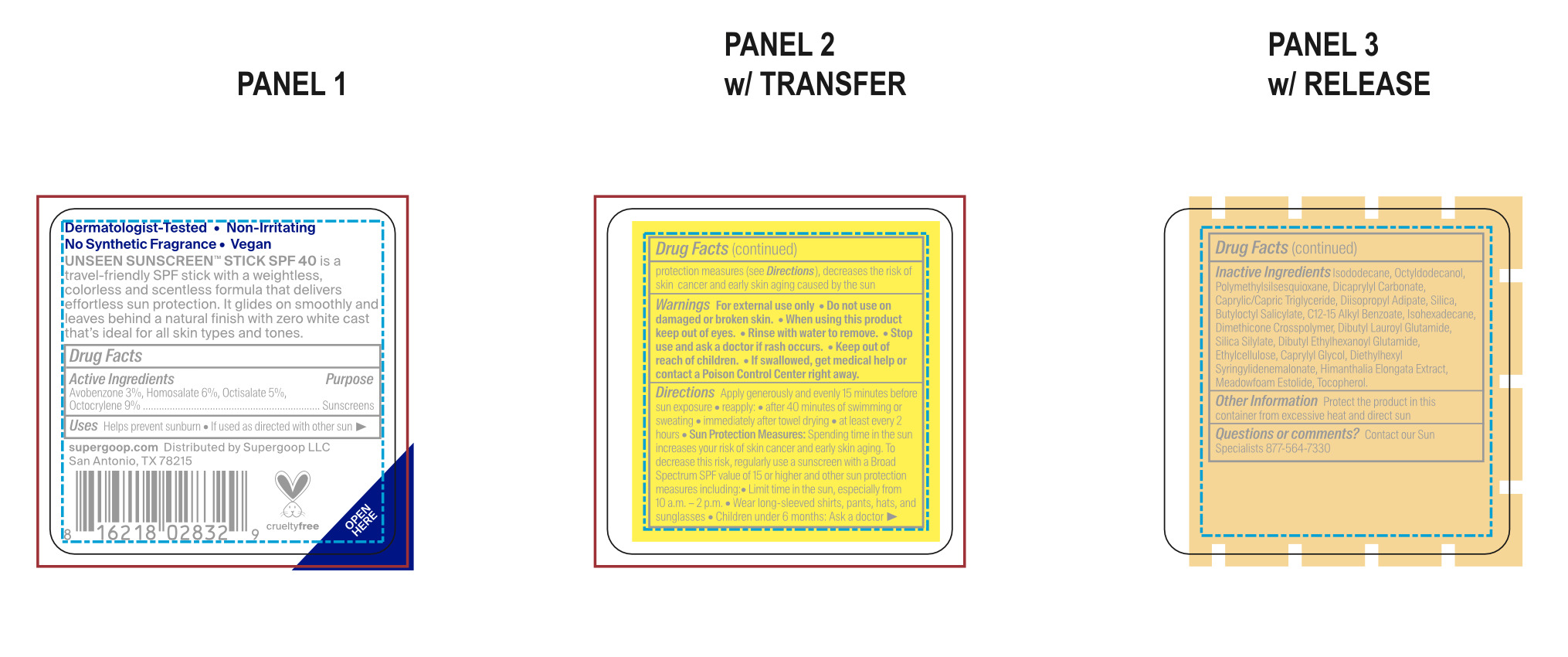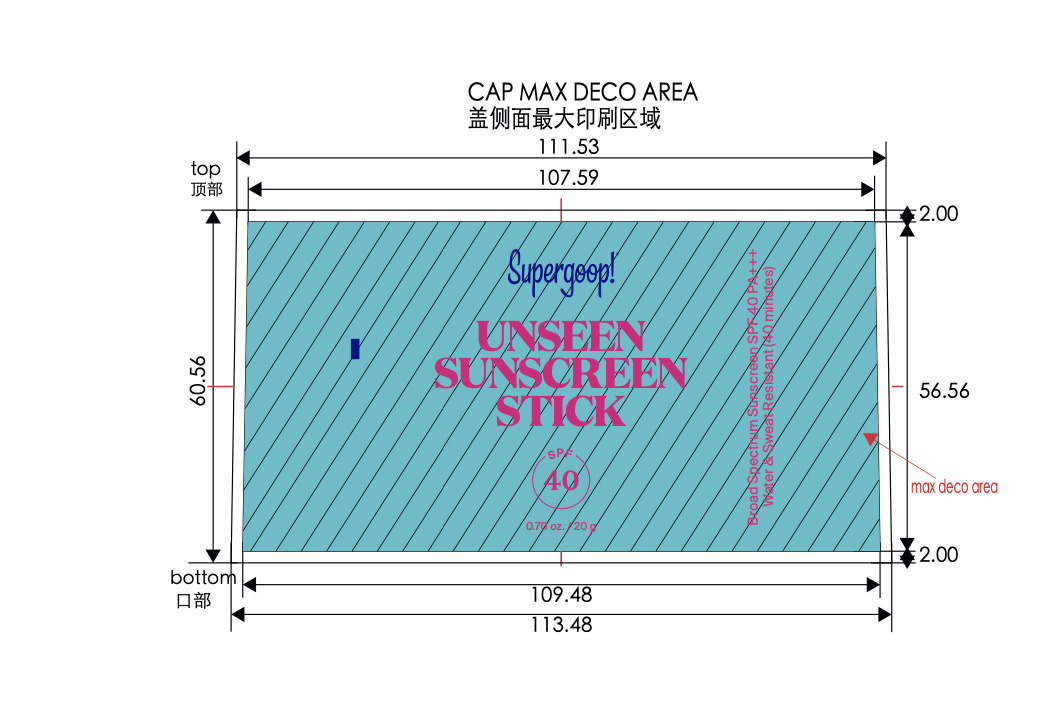 DRUG LABEL: Unseen Sunscreen Stick SPF 40
NDC: 75936-647 | Form: STICK
Manufacturer: Supergoop, LLC
Category: otc | Type: HUMAN OTC DRUG LABEL
Date: 20260109

ACTIVE INGREDIENTS: OCTOCRYLENE 9 g/100 g; AVOBENZONE 3 g/100 g; HOMOSALATE 6 g/100 g; OCTISALATE 5 g/100 g
INACTIVE INGREDIENTS: DIISOPROPYL ADIPATE; C12-15 ALKYL BENZOATE; ETHYLCELLULOSE, UNSPECIFIED; DIETHYLHEXYL SYRINGYLIDENEMALONATE; MEADOWFOAM ESTOLIDE; DIBUTYL LAUROYL GLUTAMIDE; CAPRYLIC/CAPRIC TRIGLYCERIDE; BUTYLOCTYL SALICYLATE; DIMETHICONE CROSSPOLYMER; OCTYLDODECANOL; DICAPRYLYL CARBONATE; CAPRYLYL GLYCOL; TOCOPHEROL; ISODODECANE; POLYMETHYLSILSESQUIOXANE (4.5 MICRONS); SILICON DIOXIDE; ISOHEXADECANE; DIBUTYL ETHYLHEXANOYL GLUTAMIDE; HIMANTHALIA ELONGATA

Active Ingredients

Avobenzone 3%, Homosalate 6%, Octisalate 5%, Octocrylene 9%

PURPOSE

Helps prevent sunburn

If used as directed with other sun protection measures (see Directions), decreases the risk of skin cancer and early skin aging caused by the sun

Keep out of reach of children. If product is swallowed, get medical help, or contact a poison control center right away.

WARNINGS

For External use only

Do not use on damaged or broken skin

When using this product, keep out of eyes. Rinse with water to remove

Stop use and ask a doctor if rash occurs

Directions

Apply generously and evenly 15 minutes before sun exposure

Reapply:

after 40 minutes of swimming or sweating

Immediately after towel drying

at least every 2 hours

Use a water resistant sunscreen if swimming or sweating

Sun Protection Measures: Spending time in the sun increases your risk of skin cancer and early skin aging. To decrease this risk, regularly use a sunscreen with a Broad Spectrum SPF value of 15 or higher and other sun protection measures including:

Limit time in the sun, especially from 10 a.m.- 2 p.m.

Wear long-sleeved shirts, pants, hats, and sunglasses

Children under 6 months: Ask a doctor

Inactive Ingredients:
Isododecane, Octyldodecanol, Polymethylsilsesquioxane, Dicaprylyl Carbonate, Caprylic/Capric Triglyceride, Diisopropyl Adipate, Silica, Butyloctyl Salicylate, C12-15 Alkyl Benzoate, Isohexadecane, Dimethicone Crosspolymer, Dibutyl Lauroyl Glutamide, Silica Silylate, Dibutyl Ethylhexanoyl Glutamide, Ethylcellulose, Caprylyl Glycol, Diethylhexyl Syringylidenemalonate, Himanthalia Elongata Extract, Meadowfoam Estolide, Tocopherol

PACKAGE LABEL

Unseen Stick SPF 40